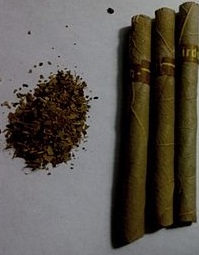 DRUG LABEL: San Su
NDC: 72942-0001 | Form: POWDER
Manufacturer: San Su
Category: otc | Type: HUMAN OTC DRUG LABEL
Date: 20190414

ACTIVE INGREDIENTS: PICRIC ACID 13 g/100 g
INACTIVE INGREDIENTS: POTASSIUM; PHOSPHORUS

Drug Facts

ACTIVE INGREDIENT

Picric acid

INACTIVE INGREDIENT

Sodium, Calcium, Phosphorus, Phytocemicals, Mineral, Potassium, Saponin, etc.

PURPOSE

Herbal cigarette

keep out of reach of the children

INDICATIONS AND USAGE

smoke the product

WARNINGS

1. For external use only.

1) Do not use over the wound and irritated skin with eczema or infections

2) Discontinue using the product if signs of irritations and/or rashes occur and seek professional medical help

2. Keep the cover closed tight after use

3. Do not put the left over contents back into the container to avoid deterioration

1) Avoid contact with eyes

2) Keep out of reach of children

3) Store in a cool and dry place, away from direct sun light

DOSAGE AND ADMINISTRATION

for external use only